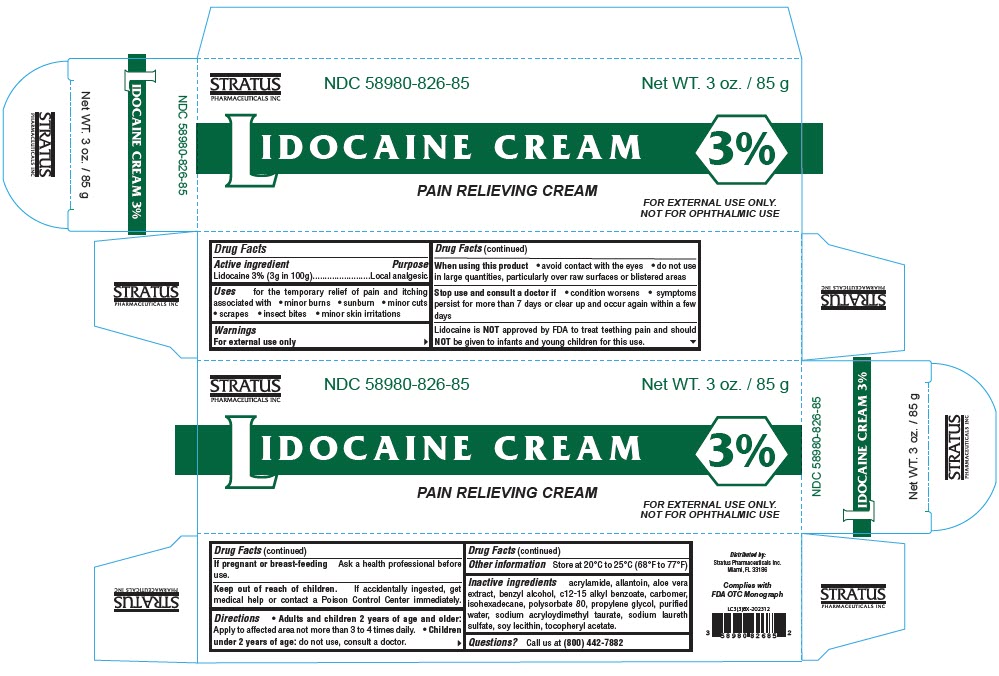 DRUG LABEL: Lidocaine
NDC: 58980-826 | Form: CREAM
Manufacturer: Stratus Pharmaceuticals Inc
Category: otc | Type: HUMAN OTC DRUG LABEL
Date: 20250612

ACTIVE INGREDIENTS: Lidocaine 30 mg/1 g
INACTIVE INGREDIENTS: Acrylamide; CARBOMER HOMOPOLYMER TYPE C (ALLYL PENTAERYTHRITOL CROSSLINKED); Allantoin; ALOE VERA LEAF; Benzyl Alcohol; ALKYL (C12-15) BENZOATE; ISOHEXADECANE; Polysorbate 80; Propylene Glycol; WATER; SODIUM ACRYLOYLDIMETHYLTAURATE; SODIUM LAURETH-3 SULFATE; SOYBEAN LECITHIN; .ALPHA.-TOCOPHEROL ACETATE

Lidocaine 3% Cream

Drug Facts

Active ingredient

Lidocaine 3% (3g in 100g)

Purpose

Local analgesic

Uses

for the temporary relief of pain and itching associated with

- minor burns
- sunburn
- minor cuts
- scrapes
- insect bites
- minor skin irritations

Warnings

For external use only

When using this product

- avoid contact with the eyes
- do not use in large quantities, particularly over raw surfaces or blistered areas

Stop use and consult a doctor if

- condition worsens
- symptoms persist for more than 7 days or clear up and occur again within a few days

Lidocaine is NOT approved by FDA to treat teething pain and should NOT be given to infants and young children for this use.

If pregnant or breast-feeding

Ask a health professional before use.

Keep out of reach of children. If accidentally ingested, get medical help or contact a Poison Control Center immediately.

Directions

- Adults and children 2 years of age and older: Apply to affected area not more than 3 to 4 times daily.
- Children under 2 years of age: do not use, consult a doctor.

Other information

Store at 20°C to 25°C (68°F to 77°F)

Inactive ingredients

acrylamide, allantoin, aloe vera extract, benzyl alcohol, c12-15 alkyl benzoate, carbomer, isohexadecane, polysorbate 80, propylene glycol, purified water, sodium acryloydimethyl taurate, sodium laureth sulfate, soy lecithin, tocopheryl acetate.

Questions?

Call us at (800) 442-7882

Distributed by:
Stratus Pharmaceuticals Inc.
Miami, FL 33186

PRINCIPAL DISPLAY PANEL - 85 g Tube Box

STRATUS
PHARMACEUTICALS INC

NDC 58980-826-85

Net WT. 3 oz. / 85 g

LIDOCAINE CREAM
3%

PAIN RELIEVING CREAM

FOR EXTERNAL USE ONLY.
NOT FOR OPHTHALMIC USE